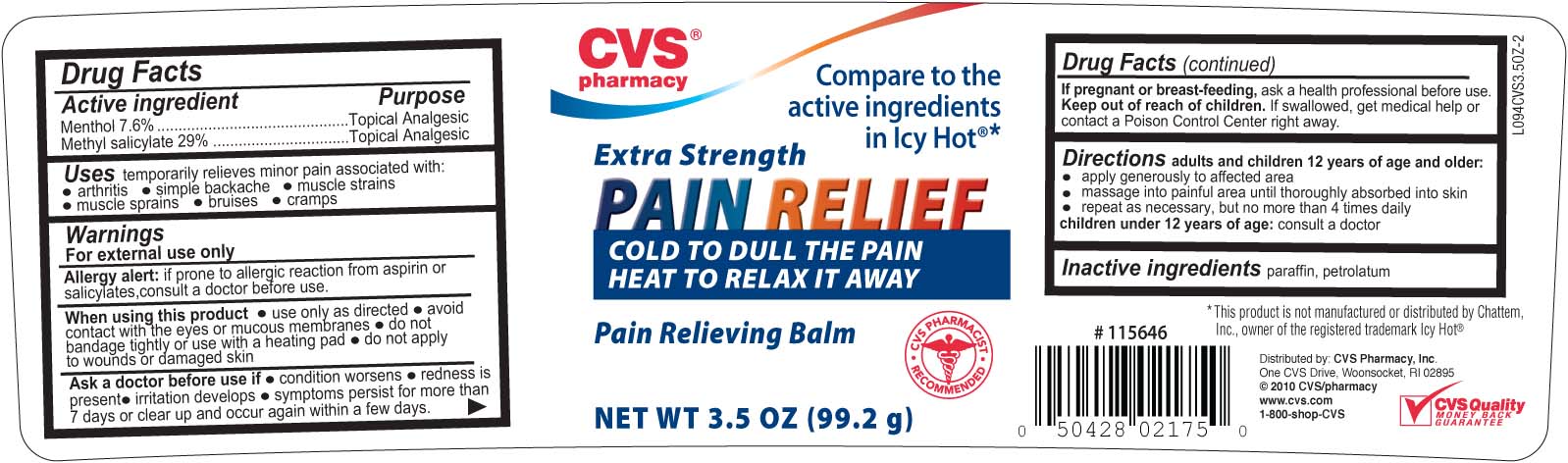 DRUG LABEL: CVS Extra Strength Pain Relief
NDC: 59779-620 | Form: GEL
Manufacturer: CVS Pharmacy
Category: otc | Type: HUMAN OTC DRUG LABEL
Date: 20100710

ACTIVE INGREDIENTS: MENTHOL 76 mg/1 g; METHYL SALICYLATE 290 mg/1 g
INACTIVE INGREDIENTS: PARAFFIN; PETROLATUM

DRUG FACTS

Active ingredient Purpose
Menthol 7.6%...................................................Topical Analgesic
Methyl Salicylate 29%.......................................Topical Analgesic

PURPOSE

Uses temporary relieves minor pain associated with:
- arthritis - simple backache - muscle strains
- muscle sprains - bruises - cramps

Keep out of reach of children. If swallowed, get medical help or contact a
Poison Control Center right away.

INDICATIONS AND USAGE

Uses temporary relieves minor pain associated with:
- arthritis - simple backache - muscle strains
- muscle sprains - bruises - cramps

Warnings
For external use only
Allergy alert: if prone to allergic reaction from aspirin or salicylates, consult a doctor before use.
When using this product - use only as directed - avoid contact with the eyes or mucous membranes
- do not bandage tightly or use with a heating pad - do not apply to wounds or damaged skin
Ask a doctor before use if - condition worsens - redness is present - irritation develops - symptoms persist
for more than 7 days or clear up and occur again within a few days.
If pregnant or breast-feeding, ask a health professional before use.
Keep out of reach of children, If swallowed, get medical help or contact a Poison Control Center right away.

DOSAGE AND ADMINISTRATION

Directions adults and children 12 years of age and older:
- apply generously to affected area
- massage into painful area until thoroughly absorbed into skin
- repeat as necessary, but no more than 4 times dily
children under 12 years of age: consult a doctor

Inactive Ingredients parrafin, petrolatum